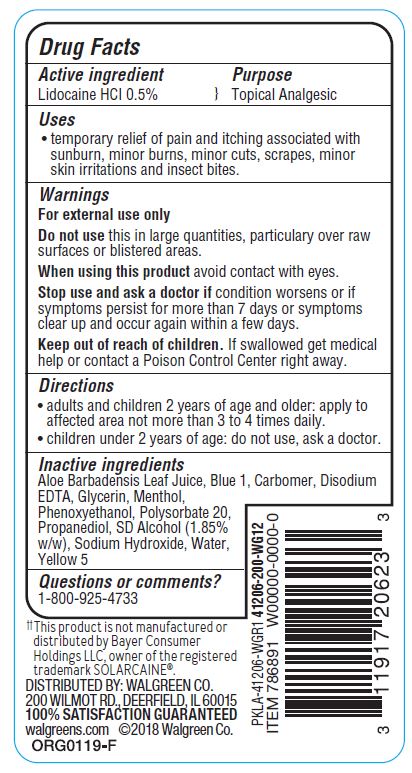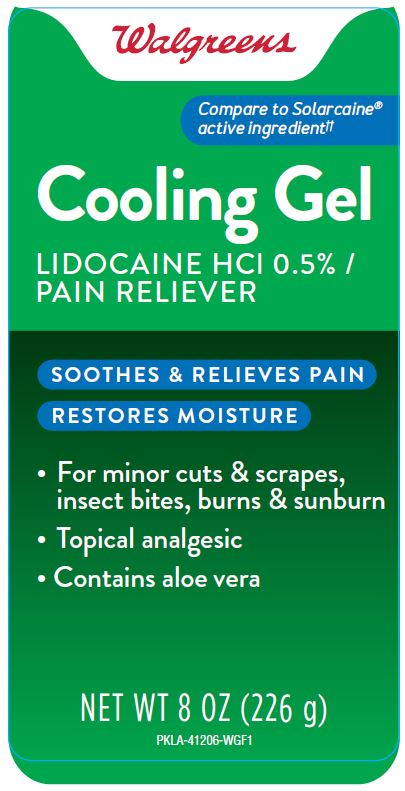 DRUG LABEL: Cooling Gel
NDC: 0363-8897 | Form: GEL
Manufacturer: Walgreen Company
Category: otc | Type: HUMAN OTC DRUG LABEL
Date: 20190715

ACTIVE INGREDIENTS: LIDOCAINE HYDROCHLORIDE 0.5 g/100 g
INACTIVE INGREDIENTS: CARBOXYPOLYMETHYLENE; GLYCERIN; MENTHOL; ALOE VERA LEAF; FD&C BLUE NO. 1; EDETATE DISODIUM; PHENOXYETHANOL; POLYSORBATE 20; PROPANEDIOL; ALCOHOL; SODIUM HYDROXIDE; WATER; BASIC YELLOW 5

WALG Cooling Gel 8OZ

Active ingredient

Lidocaine HCI 0.5%

Purpose

Topical Analgesic

Uses

• temporary relief of pain and itching associated with
sunburn, minor burns, minor cuts, scrapes, minor
skin irritations and insect bites.

Dosage & Administration

For the temporary relief of itching associated with minor skin irritations and rashes due to eczema, insect bites, and poison oak.

Warnings

For external use only

Do not use this in large quantities, particulary over raw
surfaces or blistered areas.

When using this product avoid contact with eyes.

Stop use and ask a doctor if condition worsens or if
symptoms persist for more than 7 days or symptoms
clear up and occur again within a few days.

Keep out of reach of children. If swallowed get medical
help or contact a Poison Control Center right away.

Directions

• adults and children 2 years of age and older: apply to
affected area not more than 3 to 4 times daily.
• children under 2 years of age: do not use, ask a doctor.

Inactive ingredients

Aloe Barbadensis Leaf Juice, Blue 1, Carbomer, Disodium
EDTA, Glycerin, Menthol,
Phenoxyethanol, Polysorbate 20,
Propanediol, SD Alcohol (1.85%
w/w), Sodium Hydroxide, Water,
Yellow 5

Questions or comments?

1-800-925-4733

Principal Display Panel

Walgreens

Compare to Solarcaine

active ingredient

Cooling Gel

LIDOCAINE HCl 0.5% /

PAIN RELIEVER

SOOTHES & RELIEVES PAIN

RESTORES MOISTURE

- For minor cuts & scrapes,

insect bites, burns & sunburn

- Topical analgesic
- Contains aloe vera

NET WT 8OZ (226 g)

PKLA-41206-WGF1